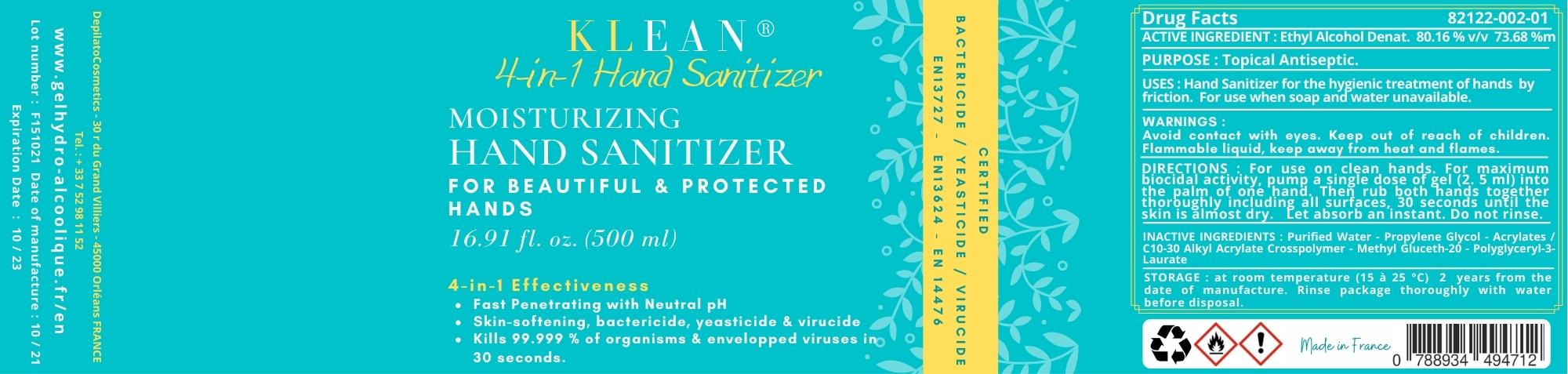 DRUG LABEL: KLEAN 4 IN 1 Sanitizer
NDC: 82122-002 | Form: GEL
Manufacturer: DepilatoCosmetics SAS
Category: otc | Type: HUMAN OTC DRUG LABEL
Date: 20211214

ACTIVE INGREDIENTS: ALCOHOL 430 g/500 g
INACTIVE INGREDIENTS: CARBOMER INTERPOLYMER TYPE A (ALLYL SUCROSE CROSSLINKED) 1.75 g/500 g; PROPYLENE GLYCOL 3.40 g/500 g; WATER 61.83 g/500 g; METHYL GLUCETH-20 1.25 g/500 g; POLYGLYCERYL-3 LAURATE 1.25 g/500 g; AMINOMETHYLPROPANOL 0.527 g/500 g; 2-AMINO-1-BUTANOL 0.003 g/500 g

Hand Sanitizer

Active Ingredient(s)

Alcohol 80,16 % v/v Denatured Alcohol. Purpose: Antiseptic

Purpose

Antiseptic, Hand Sanitizer

Use

Hand Sanitizer to help reduce bacteria that potentially can cause disease. For use when soap and water are not available.

Warnings

For external use only. Flammable. Keep away from heat or flame

Do not use

- in children less than 2 months of age
- on open skin wounds

When using this product keep out of eyes, ears, and mouth. In case of contact with eyes, rinse eyes thoroughly with water.
Stop use and ask a doctor if irritation or rash occurs. These may be signs of a serious condition.
Keep out of reach of children. If swallowed, get medical help or contact a Poison Control Center right away.

Stop use and ask a doctor if irritation or rash occurs. These may be signs of a serious condition.

Keep out of reach of children. If swallowed, get medical help or contact a Poison Control Center right away.

Directions

- Place enough product on hands to cover all surfaces. Rub hands together until dry.
- Supervise children under 6 years of age when using this product to avoid swallowing.

Other information

- Store between 15-30C (59-86F)
- Avoid freezing and excessive heat above 40C (104F)

Inactive ingredients

Purified Water - Propylene Glycol - Acrylates / C10-30 Alkyl Acrylate Crosspolymer - Methyl Gluceth-20 - Polyglyceryl-3-Laurate

Package Label - Principal Display Panel

0.5 kg (500 g) NDC: 82122-002-01